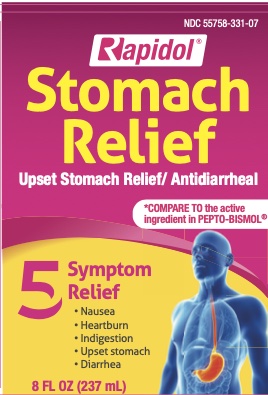 DRUG LABEL: Rapidol Stomach Relief
NDC: 55758-331 | Form: LIQUID
Manufacturer: Pharmadel LLC
Category: otc | Type: HUMAN OTC DRUG LABEL
Date: 20241118

ACTIVE INGREDIENTS: BISMUTH SUBSALICYLATE 525 mg/30 mL
INACTIVE INGREDIENTS: BENZOIC ACID; D&C RED NO. 22; D&C RED NO. 28; WATER; SACCHARIN SODIUM; SALICYLIC ACID; SODIUM SALICYLATE; XANTHAN GUM

Rapidol Stomach Relief (APTA)

Drug Facts

Active ingredient & Purposes

Active ingredient (in each 30 mL dose cup or 2 tablespoons) | Purposes
Bismuth subsalicylate 525 mg................. | Upset stomach reliever and antidiarrhea

Uses

relieves

- travelers' diarrhea
- diarrhea
- upset stomach due to overindulgence of food and drink including:
- heart burn
- indigestion
- nausea
- gas
- belching

Warnings

Reye's syndrome: Children and teenagers who have or are recovering from chicken pox or flu-like symptoms should not use this product. When using this product, if changes in behavior with nausea and vomiting occur, consult a doctor because these symptoms could be an early sign of Reye's syndrome, a rare but serious illness.

Allergy alert: contains salicylate. Do not take if you are

- allergic to salicylates (including aspirin)
- taking other salicylate products

Do not use if you have

- an ulcer
- a bleeding problem
- black or bloody stool

Ask a doctor before use if you have

- fever
- mucus in stool

Ask a doctor or pharmacist before use if you are taking any drug for

- anticoagulation (thinning of the blood)
- diabetes
- gout
- arthritis

When using this product

a temporary, but harmless, darkening of the stool and/or tongue may occur.

Slop use and ask a doctor if

- diarrhea lasts more than 2 days
- symptoms get worse or last more than 2 days
- ringing in the ears or loss of hearing occurs

If pregnant or breast feeding,

ask health professional before use.

Keep out of reach of children.

In case of overdose, get medical help or contact a Poison Control Center right away.

Directions

- shake well before use
- use dose cup or tablespoon (TBSP)
- adults and children 12 years and over: 1 dose (30 mL or 2 TBSP) every 1/2 to 1 hour or every hour as needed
- do not exceed 8 doses (240 mL or 16 TBSP) in 24 hours
- use until diarrhea stops but not more than 2 days
- drink plenty of clear fluids to help prevent dehydration caused by diarrhea
- children under 12 years: ask adoctor

Other information

- each 30 mL dose contains: magnesium45 mg, sodium 13 mg, salicylate 256 mg
- protect from freezing
- avoid excessive heat (over 104ºF or 40ºC)
- low sodium

Inactive ingredients

benzoic acid, D&C red #22, D&C red #28, flavor, purified water, saccharin sodium, salicylic acid, sodium salicylate, xanthan gum

Questions?

1-866-359-3478 (9 AM - 5 PM EST) or pharmadel.com

Distributed by:

PHARMADEL LLC.

New Castle, DE 19720

Prinicpal Display Panel

NDC 55758-331-07

Rapidol Stomach Relief 8 FL OZ (237 mL)